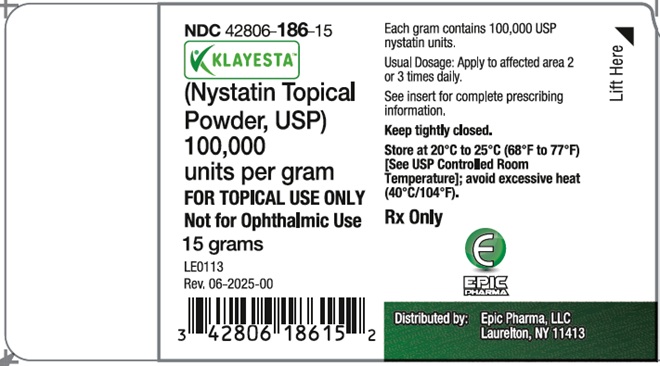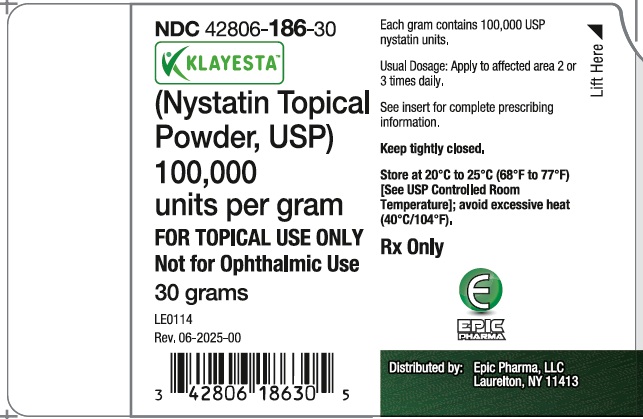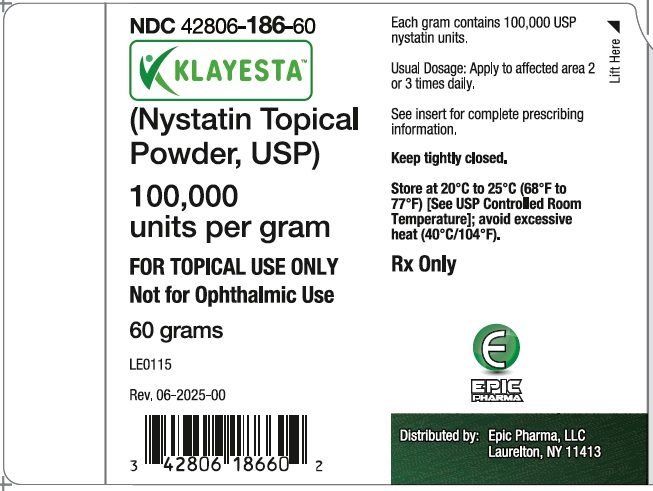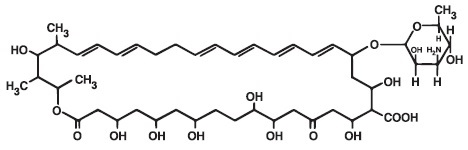 DRUG LABEL: KLAYESTA
NDC: 42806-186 | Form: POWDER
Manufacturer: Epic Pharma, LLC
Category: prescription | Type: HUMAN PRESCRIPTION DRUG LABEL
Date: 20251217

ACTIVE INGREDIENTS: NYSTATIN 100000 U/1 g
INACTIVE INGREDIENTS: MAGNESIUM STEARATE; KAOLIN

KLAYESTA (NYSTATIN TOPICAL POWDER, USP)
Rx Only

DESCRIPTION

Nystatin is a polyene antifungal antibiotic obtained from Streptomyces noursei. The molecular formula for Nystatin is C47H75NO17. The molecular weight of Nystatin is 926.09.

Structural formula:

KLAYESTA is for dermatologic use.

KLAYESTA contains 100,000 USP nystatin units per gram.

Inactive ingredients: magnesium stearate and light kaolin.

CLINICAL PHARMACOLOGY

Pharmacokinetics

KLAYESTA is not absorbed from intact skin or mucous membrane.

Microbiology

Nystatin is an antibiotic which is both fungistatic and fungicidal in vitro against a wide variety of yeasts and yeast-like fungi, including Candida albicans, C. parapsilosis, C. tropicalis, C. guilliermondi, C. pseudotropicalis, C. krusei, Torulopsis glabrata, Tricophyton rubrum, T. mentagrophytes.

Nystatin acts by binding to sterols in the cell membrane of susceptible species resulting in a change in membrane permeability and the subsequent leakage of intracellular components. On repeated subculturing with increasing levels of nystatin, Candida albicans does not develop resistance to nystatin. Generally, resistance to nystatin does not develop during therapy. However, other species of Candida (C, tropicalis, C. guilliermondi, C. krusei, and C. stellatoides) become quite resistant on treatment with nystatin and simultaneously become cross resistant to amphotericin as well. This resistance is lost when the antibiotic is removed.

Nystatin exhibits no appreciable activity against bacteria, protozoa, or viruses.

INDICATIONS AND USAGE

KLAYESTA is indicated in the treatment of cutaneous or mucocutaneous mycotic infections caused by Candida albicans and other susceptible Candida species.

KLAYESTA is not indicated for systemic, oral, intravaginal or ophthalmic use.

CONTRAINDICATIONS

KLAYESTA is contraindicated in patients with a history of hypersensitivity to any of its components.

PRECAUTIONS

General

KLAYESTA should not be used for the treatment of systemic, oral, intravaginal or ophthalmic infections.

If irritation or sensitization develops, treatment should be discontinued and appropriate measures taken as indicated. It is recommended that KOH smears, cultures, or other diagnostic methods be used to confirm the diagnosis of cutaneous or mucocutaneous candidiasis and to rule out infection caused by other pathogens.

Information for Patients

Patients using this medication should receive the following information and instructions:
1. The patient should be instructed to use this medication as directed (including the replacement of missed doses). This medication is not for any disorder other than that for which it is prescribed.
2. Even if symptomatic relief occurs within the first few days of treatment, the patient should be advised not to interrupt or discontinue therapy until the prescribed course of treatment is completed.
3. If symptoms of irritation develop, the patient should be advised to notify the physician promptly.

Laboratory Tests

If there is a lack of therapeutic response, KOH smears, cultures, or other diagnostic methods should be repeated.

Carcinogenesis, Mutagenesis, Impairment of Fertility

No long-term animal studies have been performed to evaluate the carcinogenic potential of KLAYESTA. No studies have been performed to determine the mutagenicity of nystatin or its effects on male or female fertility.

Pregnancy

Teratogenic Effects

Animal reproduction studies have not been conducted with any KLAYESTA topical preparation. It also is not known whether these preparations can cause fetal harm when used by a pregnant woman or can affect reproductive capacity. KLAYESTA should be prescribed for a pregnant woman only if the potential benefit to the mother outweighs the potential risk to the fetus.

Nursing Mothers

It is not known whether KLAYESTA is excreted in human milk. Caution should be exercised when KLAYESTA is prescribed for a nursing woman.

Pediatric Use

Safety and effectiveness have been established in the pediatric population from birth to 16 years. (See DOSAGE AND ADMINISTRATION).

Geriatric Use

Clinical studies with KLAYESTA did not include sufficient numbers of subjects aged 65 years and older to determine whether they respond differently than younger subjects. Other reported clinical experience has not identified differences in responses between elderly and younger patients, but greater sensitivity of some older individuals cannot be ruled out.

ADVERSE REACTIONS

The frequency of adverse events reported in patients using KLAYESTA is less than 0.1%. The more common events that were reported include allergic reactions, burning, itching, rash, eczema, and pain on application. (See PRECAUTIONS, General.)

DOSAGE AND ADMINISTRATION

Very moist lesions are best treated with the topical dusting powder.

Adults and Pediatric Patients (Neonates and Older)

Apply to candidal lesions two or three times daily until healing is complete. For fungal infection of the feet caused by Candida species, the powder should be dusted on the feet, as well as, in all foot wear.

HOW SUPPLIED

KLAYESTA (nystatin topical powder, USP) is off-white to light yellow powder, and is supplied as 100,000 units nystatin per gram in plastic squeeze bottles.

15 g (NDC 42806-186-15)

30 g (NDC 42806-186-30)

60 g (NDC 42806-186-60)

STORAGE

Store at 20°C to 25°C (68°F to 77°F) [see USP Controlled Room Temperature]; avoid excessive heat (40°C/104°F).

Keep tightly closed.

Distributed by:

Epic Pharma, LLC

Laurelton, NY 11413

Rev. 06-2025-00

MF186REV06/25

OS0017